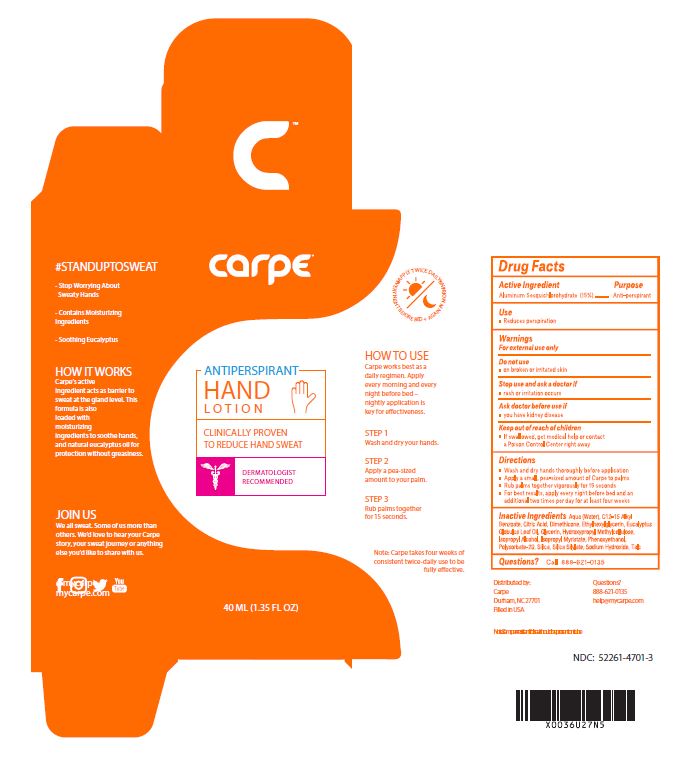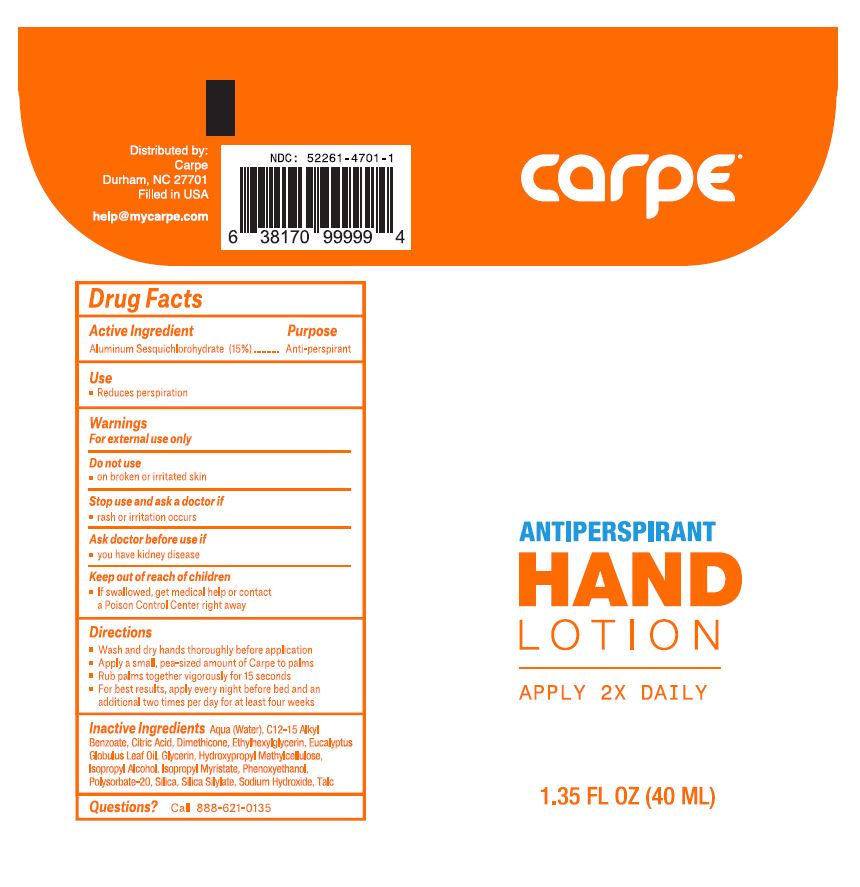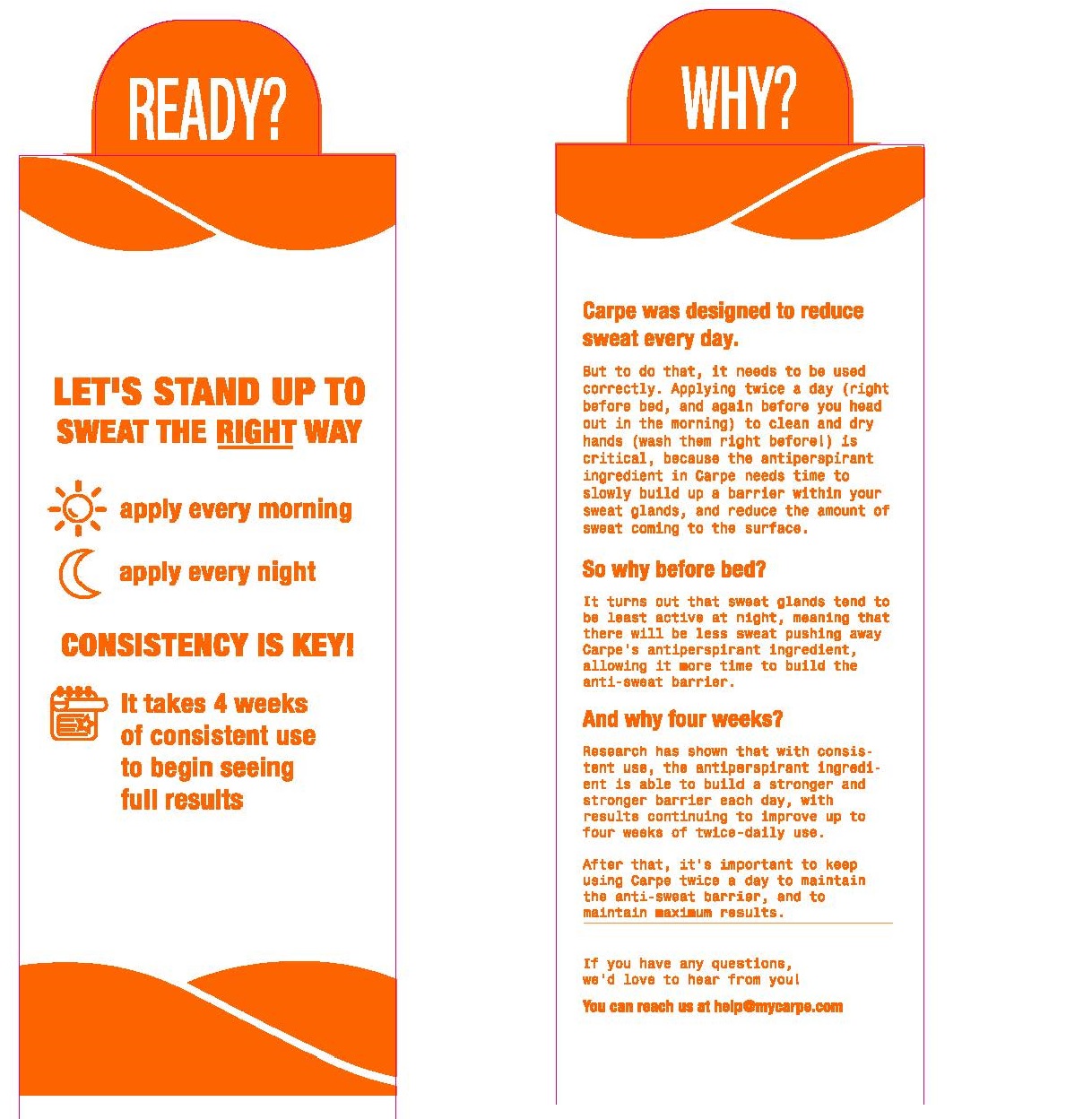 DRUG LABEL: Carpe Antiperspirant for Hands
NDC: 52261-4701 | Form: Lotion
Manufacturer: Cosco International, Inc.
Category: otc | Type: HUMAN OTC DRUG LABEL
Date: 20250331

ACTIVE INGREDIENTS: Aluminum Sesquichlorohydrate 0.15048 kg/1 kg
INACTIVE INGREDIENTS: water; isopropyl alcohol; silicon dioxide; HEXAMETHYLDISILAZANE; talc; polysorbate 20; dimethicone 350; ALKYL (C12-15) BENZOATE; phenoxyethanol; ISOPROPYL MYRISTATE; eucalyptus oil; glycerin; hypromellose 2208 (60000 MPA.S); sodium hydroxide; citric acid monohydrate; ethylhexylglycerin

Drug Facts

Active Ingredient Purpose
Aluminum Sesquicholorhydrate 15% .......................Antiperspirant

PURPOSE

Anti-perspirant

Use

- Reduces perspiration

Warnings

For external use only

Do not use

- on broken or irritated skin

Stop use and ask a doctor if

- rash or irritation occurs

Ask doctor before use if

- you have kidnet disease

Keep out of reach of children

- If swallowed, get medical help or contact a Poison Control Center right away

Directions

- Wash and dry hands throughly before application
- Apply a small, pea-sized amount of Carpe to palms
- Rub palms together vigorously for a minimum of 15 seconds
- For best results, apply every night before bed and an additional two times per day for at least four weeks

Inactive ingredients

Aqua (Water), C12-15 Alkyl Benzoate, Citric Acid, Dimethicone, Ethylhexylglycerin, Eucalyptus Globulus Leaf Oil, Glycerin, Hydroxypropyl Methylcellulose, Isopropyl Alcohol, Isopropyl Myristate, Phenoxyethanol, Polysorbate-20, Silica, Silica Silylate, Sodium Hydroxide, Talc

Questions?

Call 888-621-0135